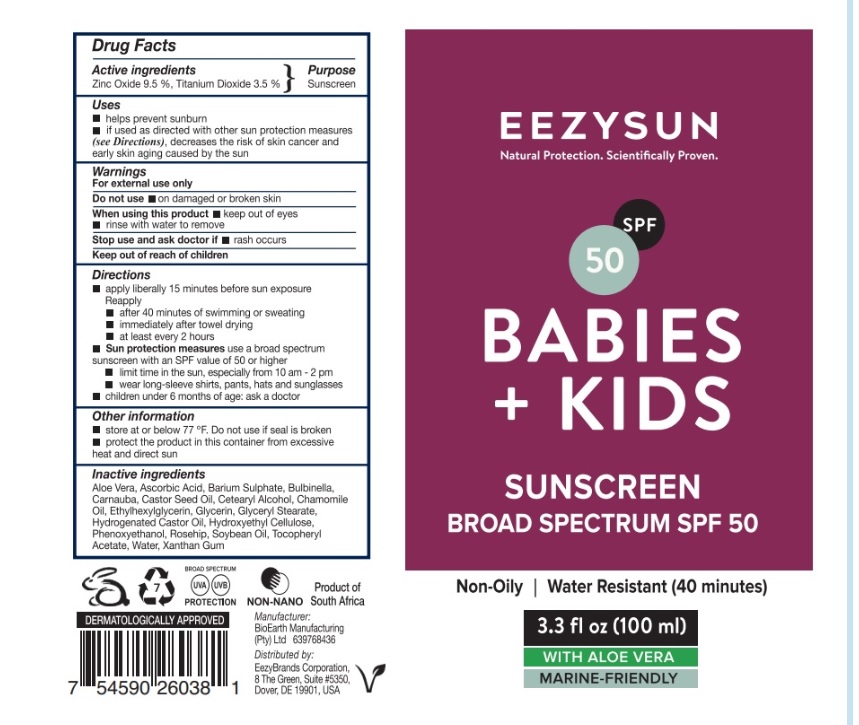 DRUG LABEL: Eezysun SPF50 Babies and Kids
NDC: 70116-013 | Form: CREAM
Manufacturer: BIO EARTH MANUFACTURING (PTY) LTD
Category: otc | Type: HUMAN OTC DRUG LABEL
Date: 20241024

ACTIVE INGREDIENTS: TITANIUM DIOXIDE 3.5 g/100 mL; ZINC OXIDE 9.5 g/100 mL
INACTIVE INGREDIENTS: ALOE VERA LEAF POLYSACCHARIDES; ASCORBIC ACID; BARIUM SULFATE; BULBINE FRUTESCENS WHOLE; CHAMOMILE FLOWER OIL; CARNAUBA WAX; CASTOR OIL; CETOSTEARYL ALCOHOL; ETHYLHEXYLGLYCERIN; GLYCERIN; GLYCERYL MONOSTEARATE; HYDROGENATED CASTOR OIL; HYDROXYETHYL CELLULOSE, UNSPECIFIED; PHENOXYETHANOL; ROSA MOSCHATA OIL; SOYBEAN OIL; .ALPHA.-TOCOPHEROL ACETATE; WATER; XANTHAN GUM

Active ingredients

Titanium Dioxide 3.5%, Zinc Oxide 9.5%

Purpose

Topical SPF50 Sun Cream for the prevention of sun burn

Uses

Helps prevents sunburn
if used as directed with other sun protection measures (see Directions), decreases the risk of skin cancer and early skin aging caused by the sun

Warnings

For external use only
Do not use ondamaged or broken skin
When using this productkeep out of eyes.
rinse with water to remove
Stop use and ask doctor ifrash occurs
Keep out of reach of children

Direction

Apply liberally 15 minutes before sun exposure
Reapply after 40 minutes if swimming or sweating
immediately after towel drying
at least every two hours
Sun protection measuresuse a broad-spectrum sunscreen with an SPF value of 50 or higher
limit time in the sun, especially from 10am - 2pm
wear long-sleeve shirts, pants, hats, sunglasses
Children under 6 months of age: ask a doctor

Other information

Store at or below 77℉. Do not use if seal is broken
Protect the product in this container from excessive heat and direct sun

Inactive ingredients

Aloe Vera, Ascorbic Acid, Barium Sulphate, Bulbinella, Carnauba, Castor Seed Oil, Cetearyl Alcohol, Chamomile Oil, Ethylhexylglycerin, Glycerin, Glyceryl Stearate, Hydrogenated Castor Oil, Hydroxyethyl Cellulose, Phenoxyethanol, Rosehip, Soybean Oil, Tocopheryl Acetate, Water, Xanthan Gum